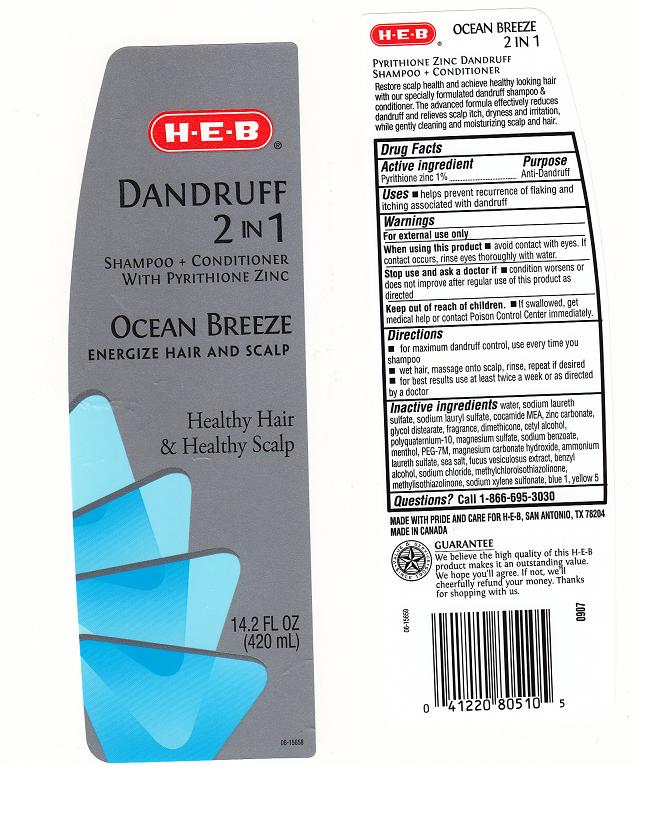 DRUG LABEL: HEB
NDC: 37808-424 | Form: SHAMPOO
Manufacturer: HEB
Category: otc | Type: HUMAN OTC DRUG LABEL
Date: 20111223

ACTIVE INGREDIENTS: PYRITHIONE ZINC 1 mL/100 mL
INACTIVE INGREDIENTS: WATER; SODIUM LAURETH SULFATE; SODIUM LAURYL SULFATE; COCO MONOETHANOLAMIDE; ZINC CARBONATE; GLYCOL DISTEARATE; DIMETHICONE; CETYL ALCOHOL; POLYQUATERNIUM-10 (400 CPS AT 2%); MAGNESIUM SULFATE, UNSPECIFIED; SODIUM BENZOATE; MENTHOL; POLYETHYLENE GLYCOL 7000; MAGNESIUM CARBONATE HYDROXIDE; AMMONIUM LAURETH-3 SULFATE; SEA SALT; FUCUS VESICULOSUS; BENZYL ALCOHOL; SODIUM CHLORIDE; METHYLCHLOROISOTHIAZOLINONE; METHYLISOTHIAZOLINONE; SODIUM XYLENESULFONATE; FD&C BLUE NO. 1; FD&C YELLOW NO. 5

DRUG FACTS

ACTIVE INGREDIENT

PYRITHIONE ZINC 1%

PURPOSE

ANTI-DANDRUFF

USES

HELPS PREVENT RECURRENCE OF FLAKING AND ITCHING ASSOCIATED WITH DANDRUFF

WARNINGS

FOR EXTERNAL USE ONLY

WHEN USING THIS PRODUCT

AVOID CONTACT WITH EYES. IF CONTACT OCCURS, RINSE EYES THOROUGHLY WITH WATER.

STOP USE AND ASK A DOCTOR IF

CONDITION WORSONS OR DOES NOT IMPROVE AFTER REGULAR USE OF THIS PRODUCT AS DIRECTED

KEEP OUT OF REACH OF CHILDREN

IF SWALLOWED GET MEDICAL HELP OR CONTACT POISON CONTROL CENTER IMMEDIATELY

DIRECTIONS

FOR MAXIMUM DANDRUFF CONTROL, USE EVERY TIME YOU SHAMPOO

WET HAIR, MASSAGE ONTO SCALP, RINSE, REPEAT IF DESIRED

FOR BEST RESULTS USE AT LEAST TWICE A WEEK OR AS DIRECTED BY A DOCTOR

INACTIVE INGREDIENTS

WATER, SODIUM LAURETH SULFATE, SODIUM LAURYL SULFATE, COCAMIDE DEA, ZINC CARBONATE, GLYCOL DISTEARATE, FRAGRANCE, DIMETHICONE, CETYL ALCOHOL, POLYQUATERNIUM-10, MAGNESIUM SULFATE, SODIUM BENZOATE, MENTHOL, PEG-7M, MAGNESIUM CARBONATE HYDROXIDE, AMMONIUM LAURETH SULFATE, SEA SALT, FUCUS VESICULOSUS EXTRACT, BENZYL ALCOHOL, SODIUM CHLORIDE, METHYLCHLOROISOTHIAZOLINONE, METHYLISOTHIAZOLINONE, SODIUM XYLENE SULFONATE, BLUE 1, YELLOW 5